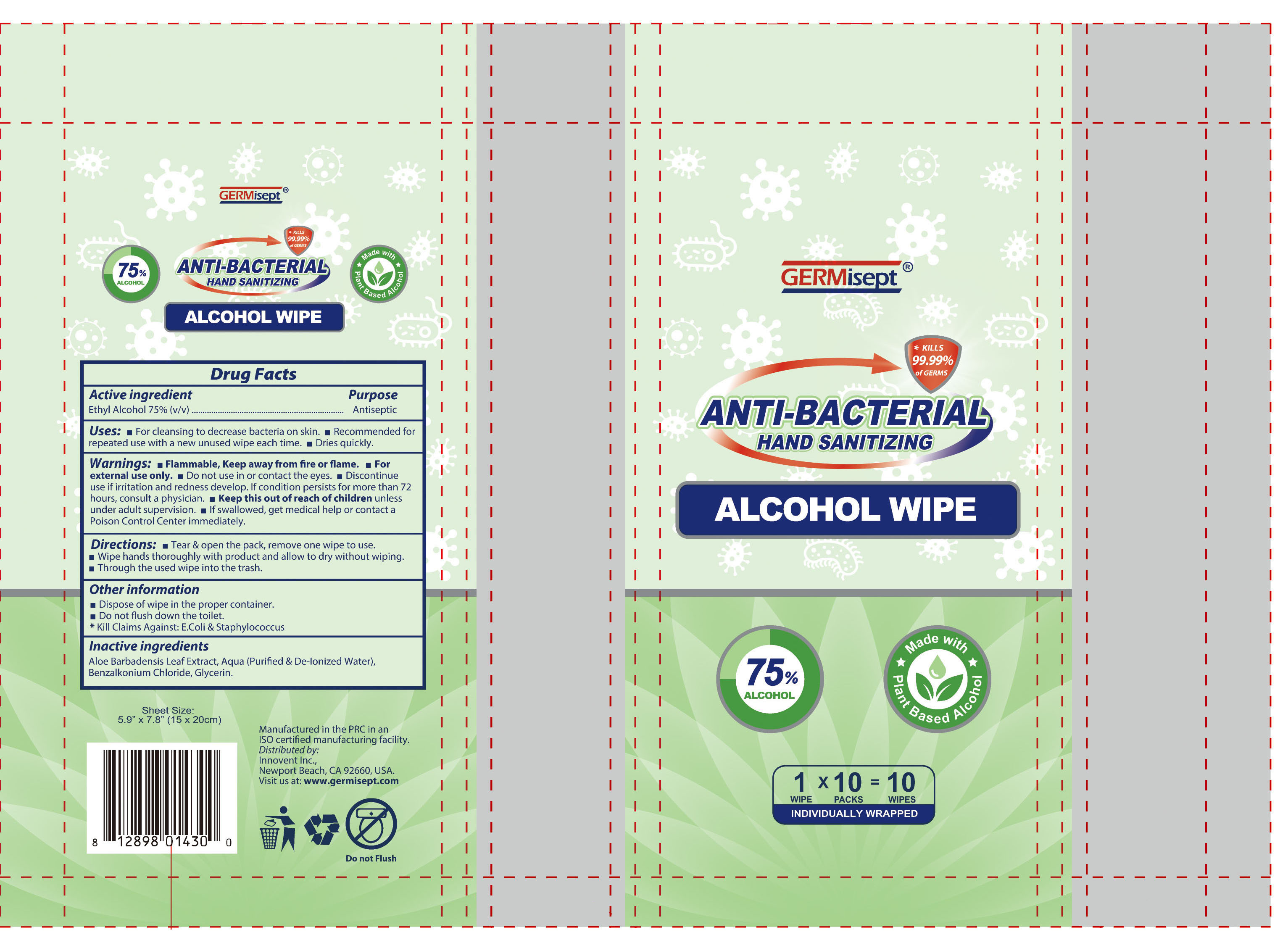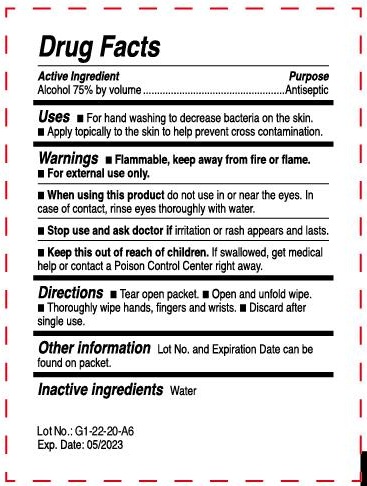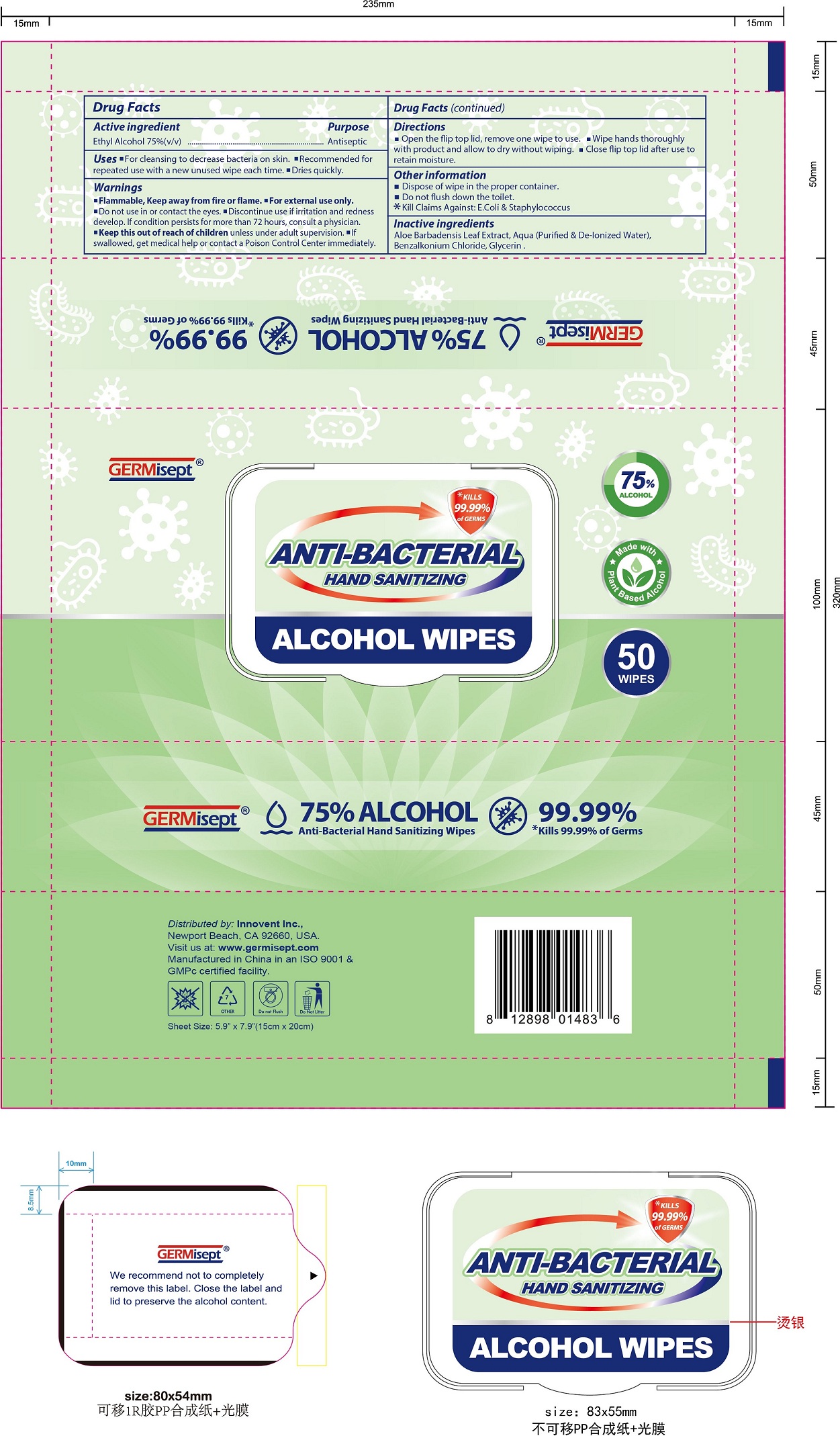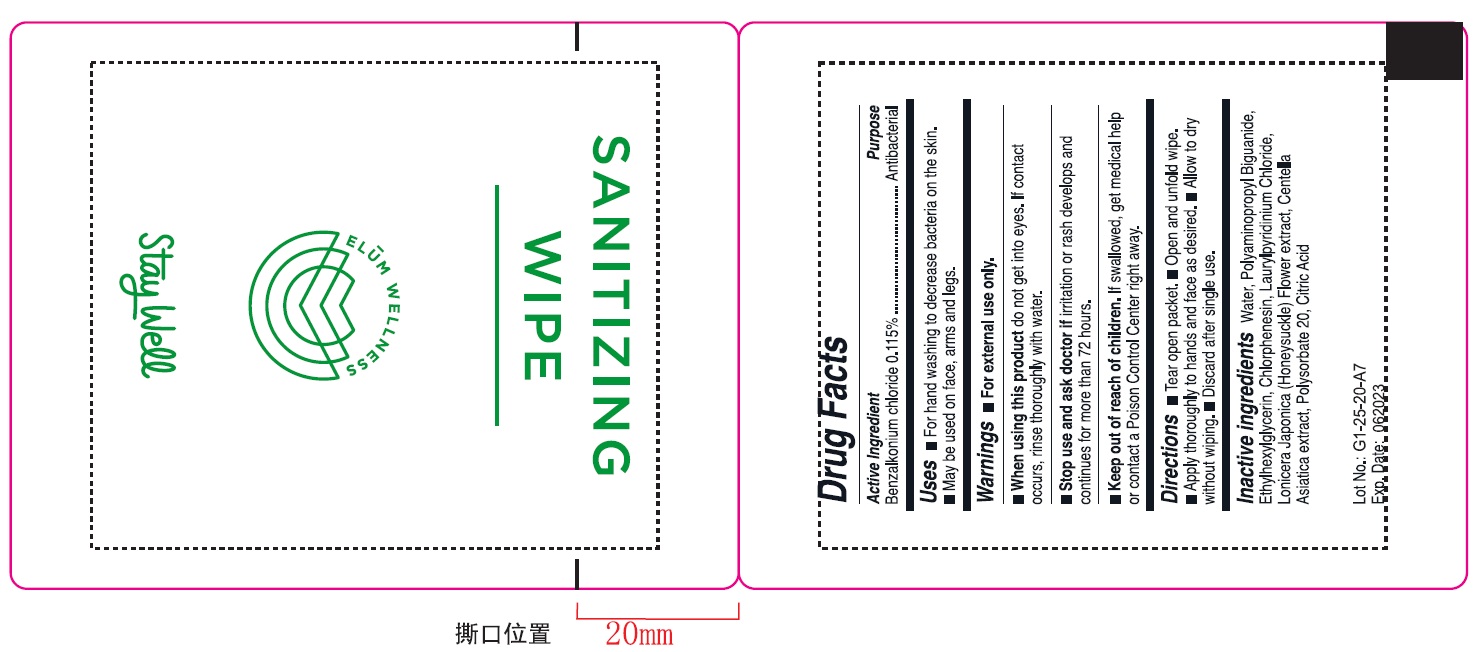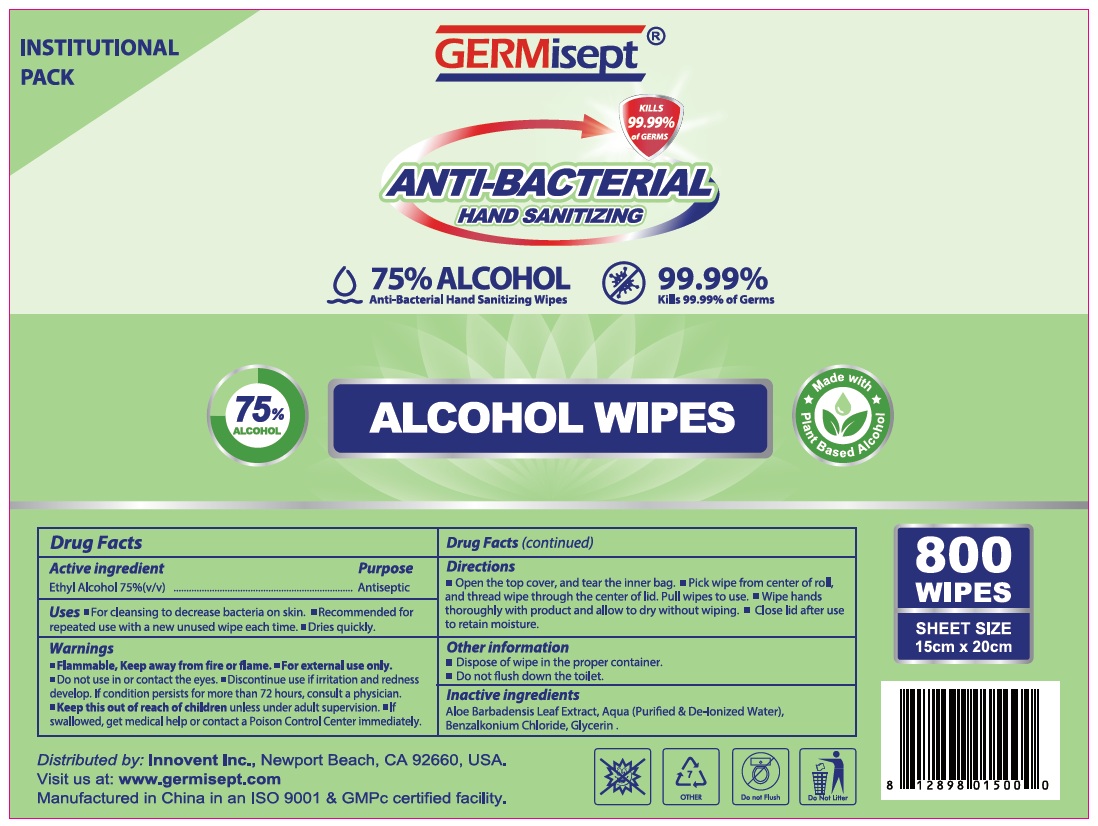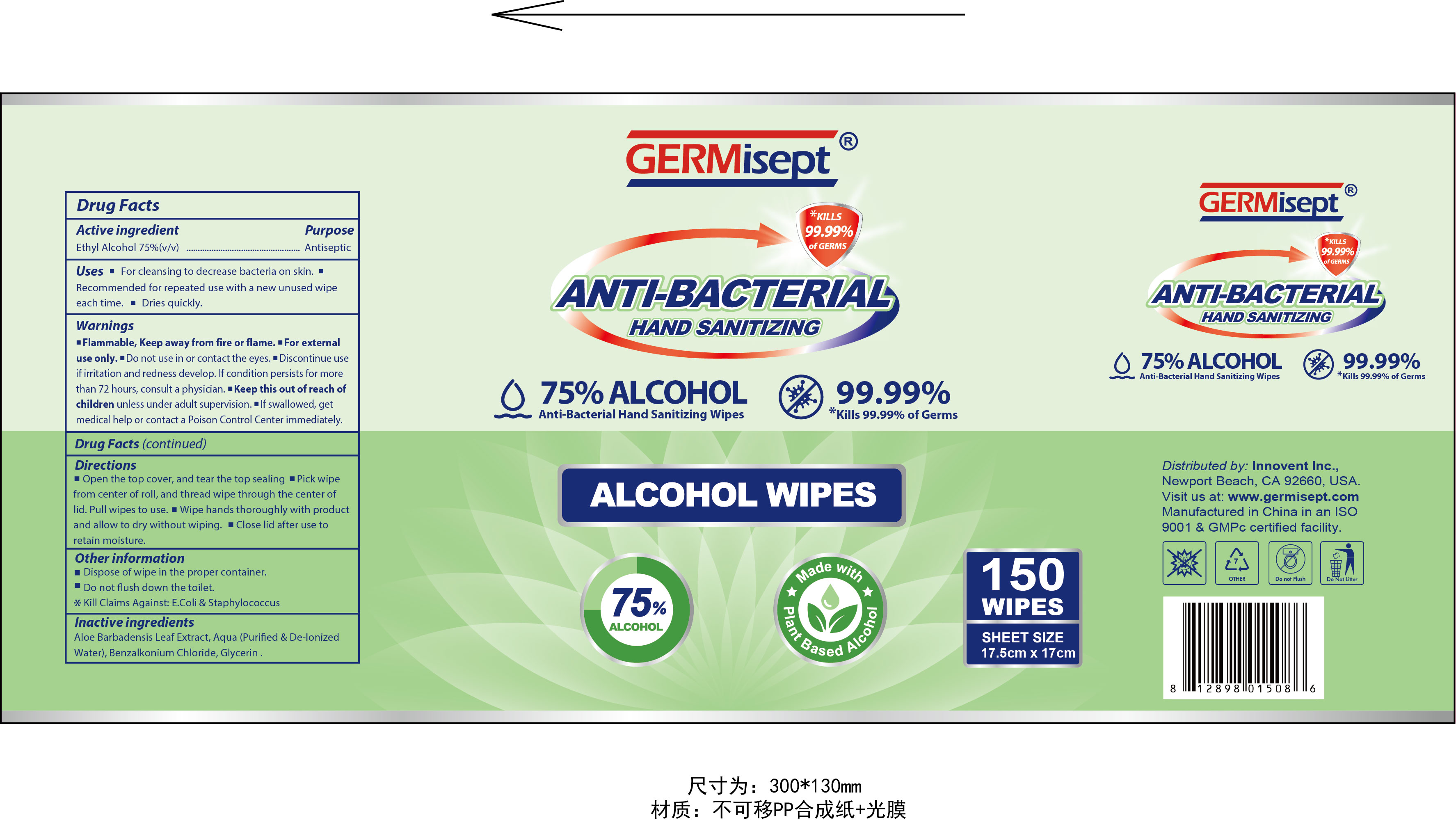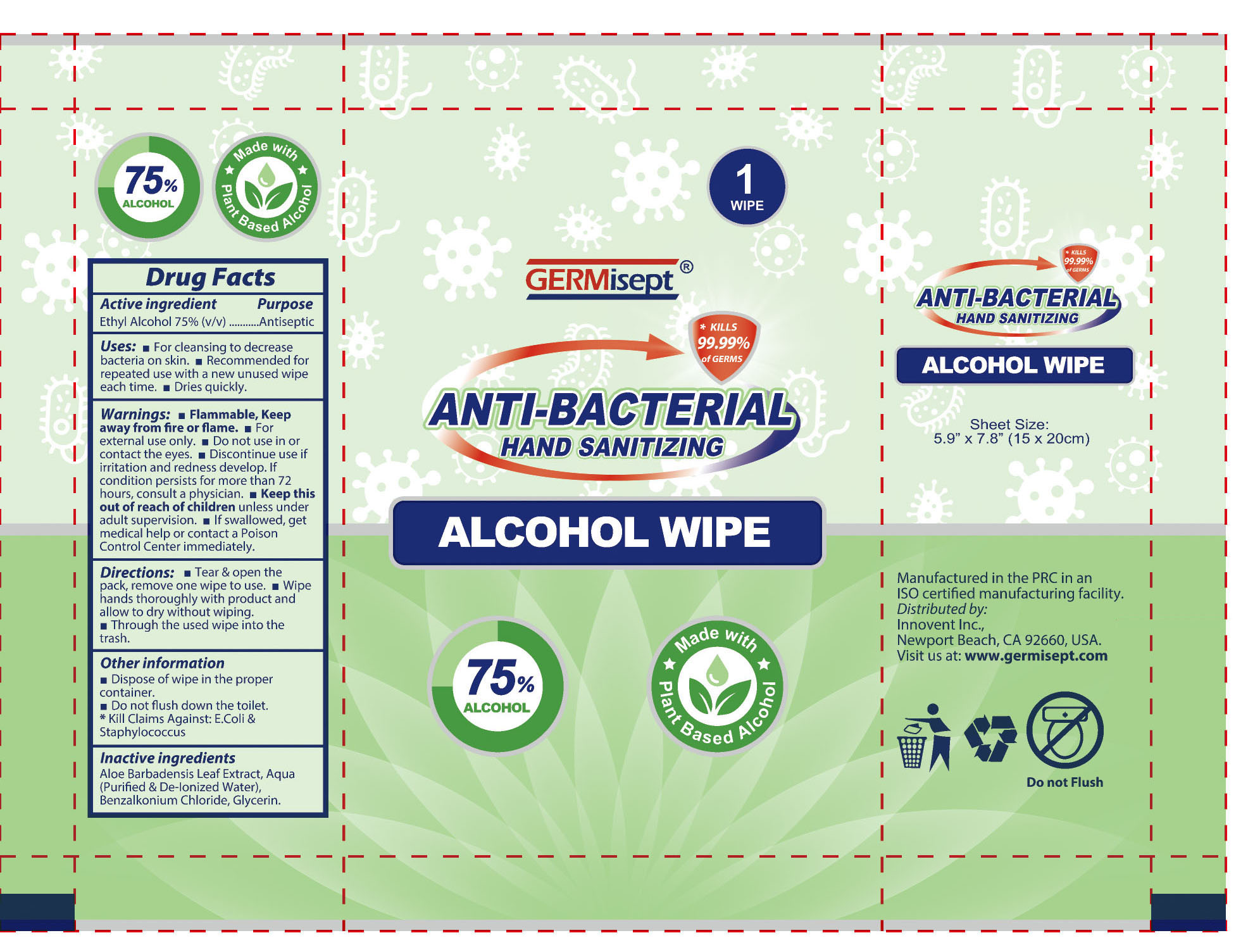 DRUG LABEL: Alcohol Wet Wipes
NDC: 78627-001 | Form: SWAB
Manufacturer: Suzhou Borage Medical Technology Co.,Ltd.
Category: otc | Type: HUMAN OTC DRUG LABEL
Date: 20211022

ACTIVE INGREDIENTS: ALCOHOL 75 1/100 1
INACTIVE INGREDIENTS: GLYCERIN; BENZALKONIUM CHLORIDE; WATER; ALOE

ACTIVE INGREDIENT

Alcohol 75% by volume................Antiseptic

INDICATIONS AND USAGE

For hand washing to decrease bacteria on the skin.

Apply topically to the skin to help prevent cross contamination.

WARNINGS

- Flammable, keep away from fire or flame.
- For external only.
- When using this product do not use in or near the eyes. In case of contact. rinse eyes throughly with water.
- Stop and ask doctor If irritation or rash appears and lasts.
- Keep this out of reach of children. If swallowed. get medical help or contact a Poison Control Center right away.

KEEP OUT OF REACH OF CHILDREN

If swallowed, get medical help or contact a Poison Control Center right away.

PURPOSE

For hand washing to decrease bacteria on the skin.

DOSAGE AND ADMINISTRATION

- Tear open packet
- Open and unfold wipe
- Thoroughly wipe hands, fingers and wrists.
- Discard after single use.

INACTIVE INGREDIENT

Water